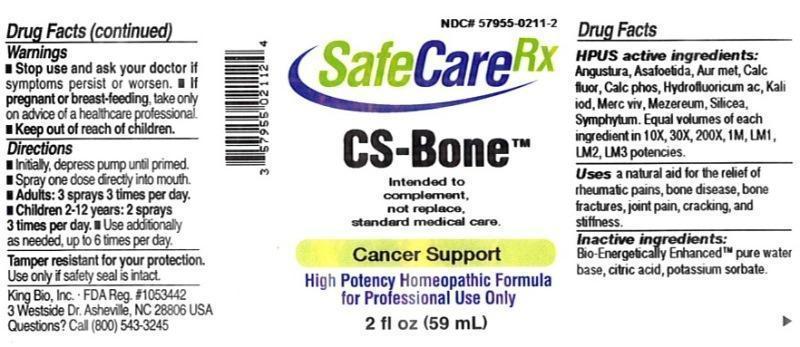 DRUG LABEL: CS Bone
NDC: 57955-0211 | Form: LIQUID
Manufacturer: King Bio Inc.
Category: otc | Type: HUMAN OTC DRUG LABEL
Date: 20150710

ACTIVE INGREDIENTS: ANGOSTURA BARK 10 [hp_X]/59 mL; ASAFETIDA 10 [hp_X]/59 mL; GOLD 10 [hp_X]/59 mL; CALCIUM FLUORIDE 10 [hp_X]/59 mL; TRIBASIC CALCIUM PHOSPHATE 10 [hp_X]/59 mL; HYDROFLUORIC ACID 10 [hp_X]/59 mL; POTASSIUM IODIDE 10 [hp_X]/59 mL; MERCURY 10 [hp_X]/59 mL; DAPHNE MEZEREUM BARK 10 [hp_X]/59 mL; SILICON DIOXIDE 10 [hp_X]/59 mL; COMFREY ROOT 10 [hp_X]/59 mL
INACTIVE INGREDIENTS: WATER; ANHYDROUS CITRIC ACID; POTASSIUM SORBATE

CS Bone™

ACTIVE INGREDIENT

Drug Facts__________________________________________________________________________________________________________

HPUS active ingredients: Angustura vera, Asafoetida, Aurum metallicum, Calcarea fluorica, Calcarea phosphorica, Hydrofluoricum acidum, Kali iodatum, Mercurius vivus, Mezereum, Silicea, Symphytum officinale. Equal volumes of each ingredient in 10X, 30X, 200X, 1M, LM1, LM2, LM3 potencies.

INDICATIONS AND USAGE

Uses a natural aid for the relief of rheumatic pains, bone disease, bone fractures, joint pain, cracking, and stiffness.

INACTIVE INGREDIENT

Inactive Ingredients: Bio-Energetically Enhanced™ pure water, citric acid and potassium sorbate.

Warnings

- Stop use and ask your doctor if symptoms persist or worsen.
- If pregnant or breast-feeding, take only on advice of a healthcare professional.

- Keep out of reach of children.

Directions

- Initially, depress pump until primed.
- Spray one dose directly into mouth.
- Adults 12 and up: 3 sprays 3 times per day.
- Children 2-12 years: 2 sprays 3 times per day.
- Use additionally as needed, up to 6 times per day.

OTHER SAFETY INFORMATION

Tamper resistant for your protection. Use only if safety seal is intact.

PURPOSE

Uses a natural aid for the relief of:

- rheumatic pains
- bone disease
- bone fractures
- joint pain
- cracking
- stiffness